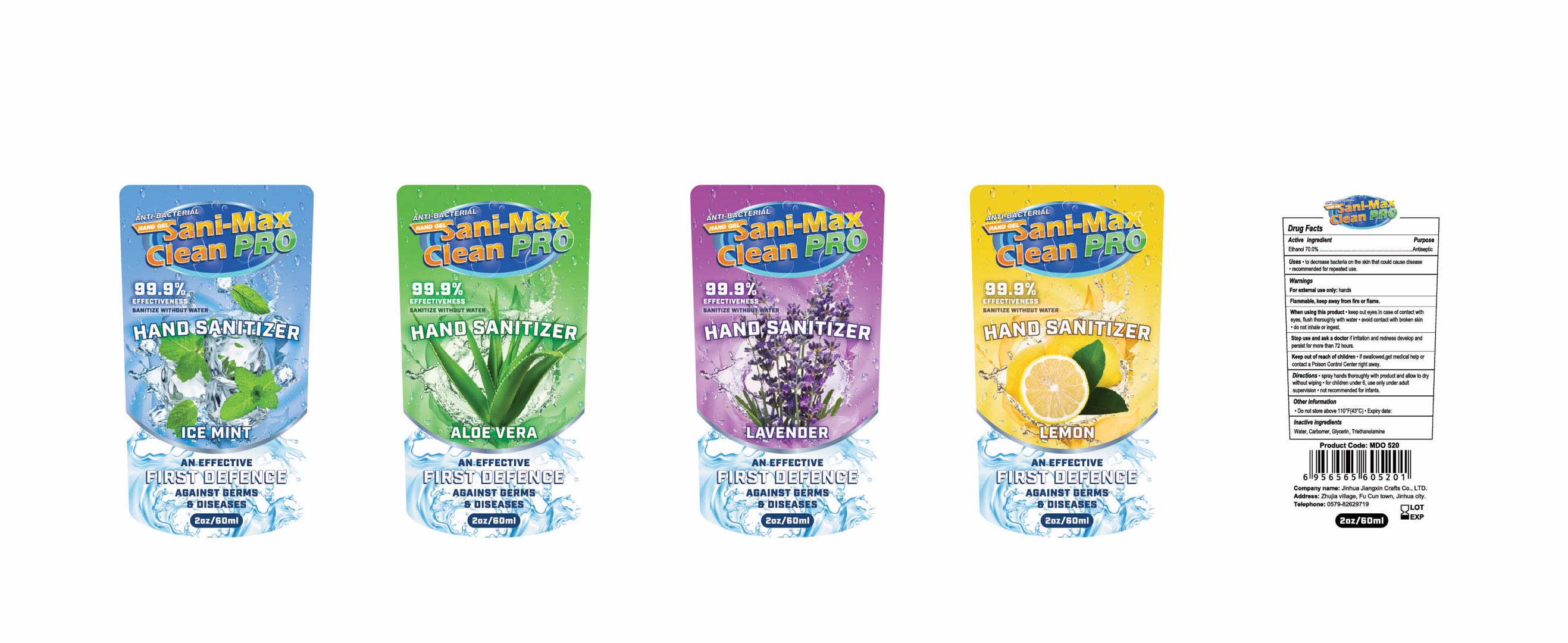 DRUG LABEL: Hand Sanitizer
NDC: 78877-001 | Form: GEL
Manufacturer: Jinhua Jiangxin Crafts Co., Ltd.
Category: otc | Type: HUMAN OTC DRUG LABEL
Date: 20200914

ACTIVE INGREDIENTS: ALCOHOL 70 mL/100 mL
INACTIVE INGREDIENTS: WATER; GLYCERIN; TROLAMINE; CARBOMER HOMOPOLYMER, UNSPECIFIED TYPE

78877-001 70% Alcohol Hand Sanitizer

Active Ingredient

Ethanol 70.0%

Purpose

Antiseptic

Use

● to decrease bacteria on the skin that could cause disease
●recommended for repeated use.

WARNINGS

For extermal use only; hands
Flammable, keep away from fire or flame.
When using this product●keep out eyes.In case of contact with
eyes, fush thoroughly with water●avoid contact with broken skin
●do not inhale or ingest.
Stop use and ask a doctor if iritation and redness develop and
persist for more than 72 hours.

Keep out of reach of children
If swallowed , get medical help or contact a Poison Control Center right away

Directions

Directions spray hands thoroughly with product and allow to dry
without wiping ● for children under 6, use only under adult
supervision ●not recommended for infants.

Inactive ingredients

Water, Carbomer, Glycerin, Triethanolamine